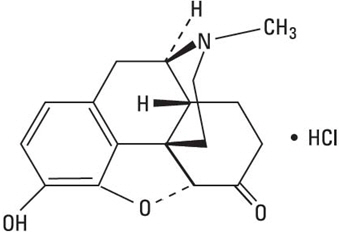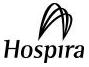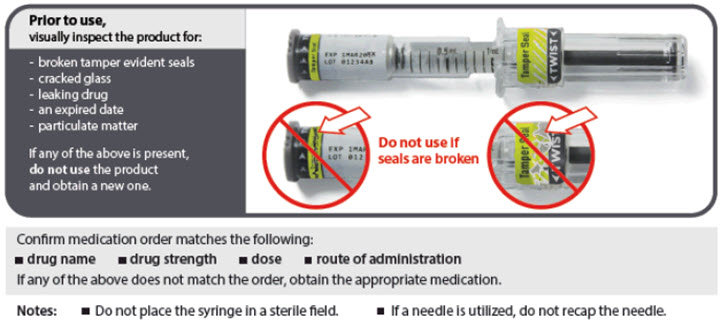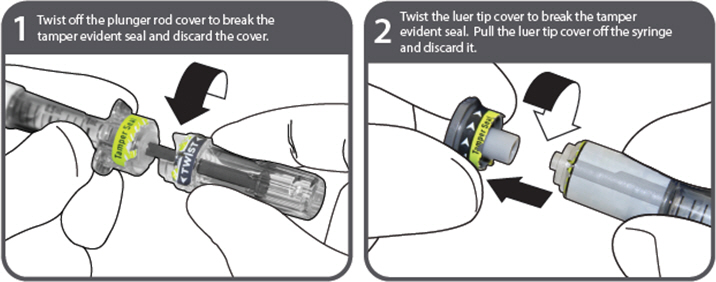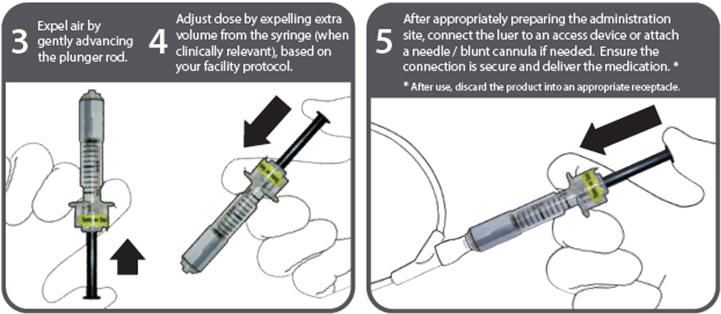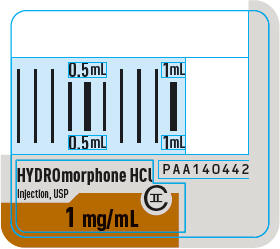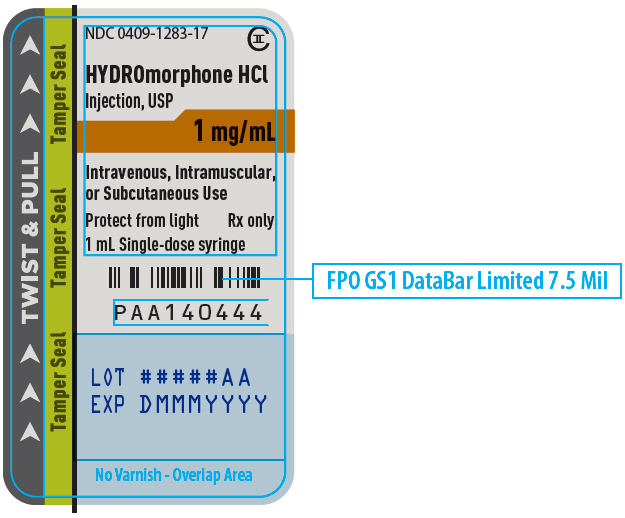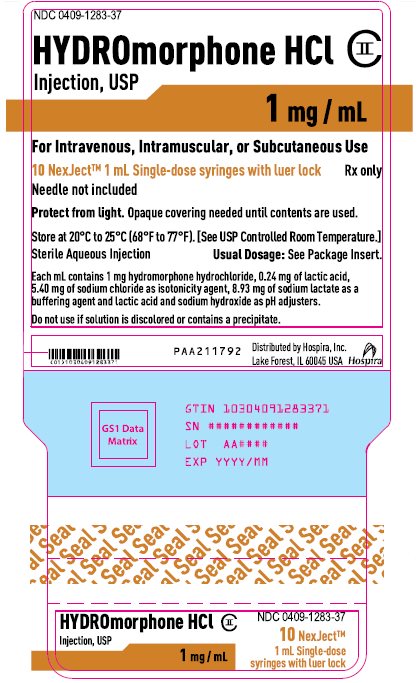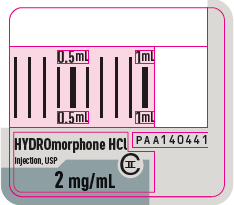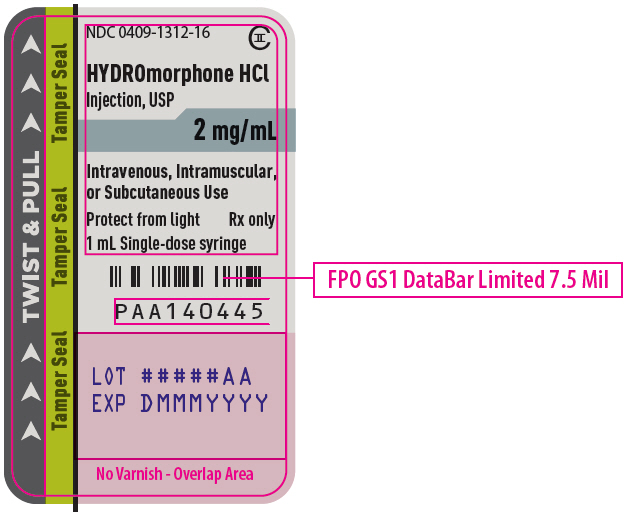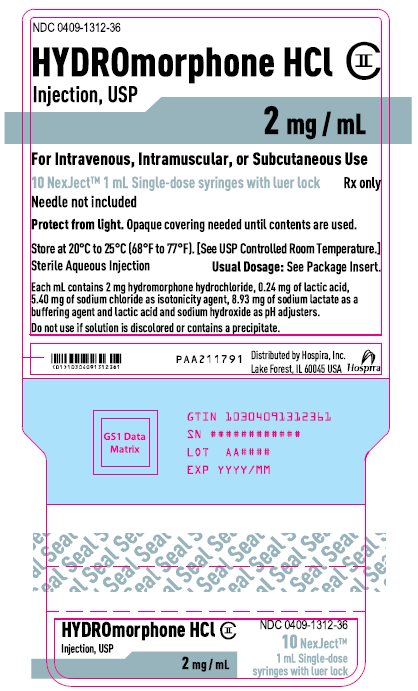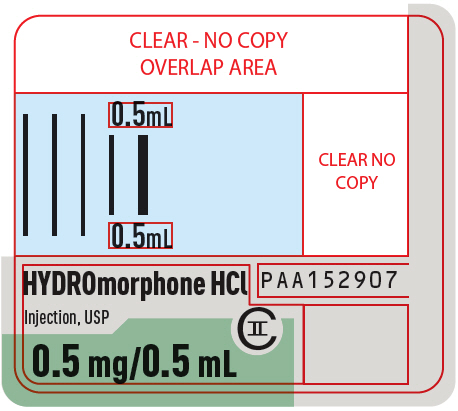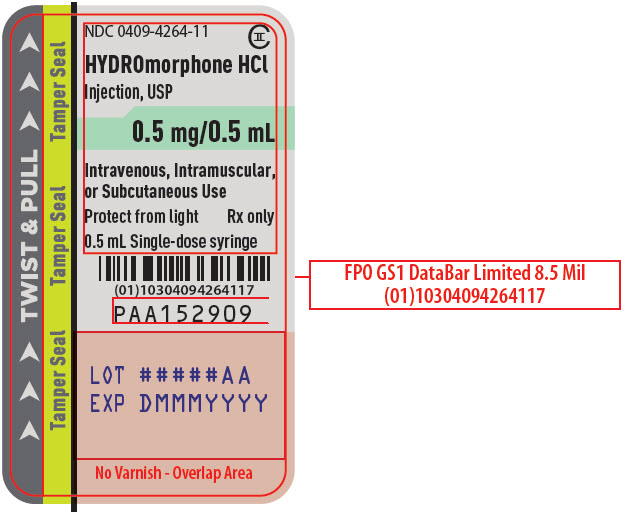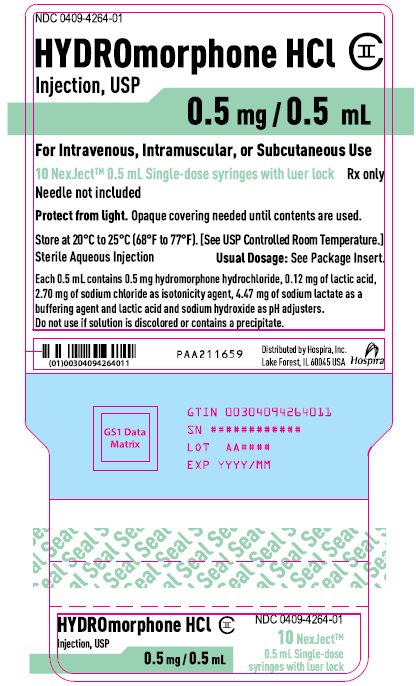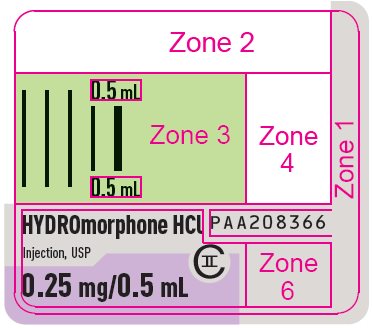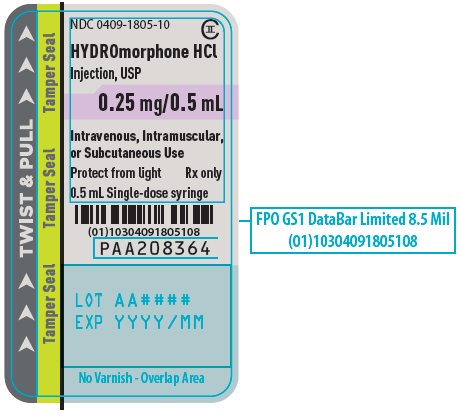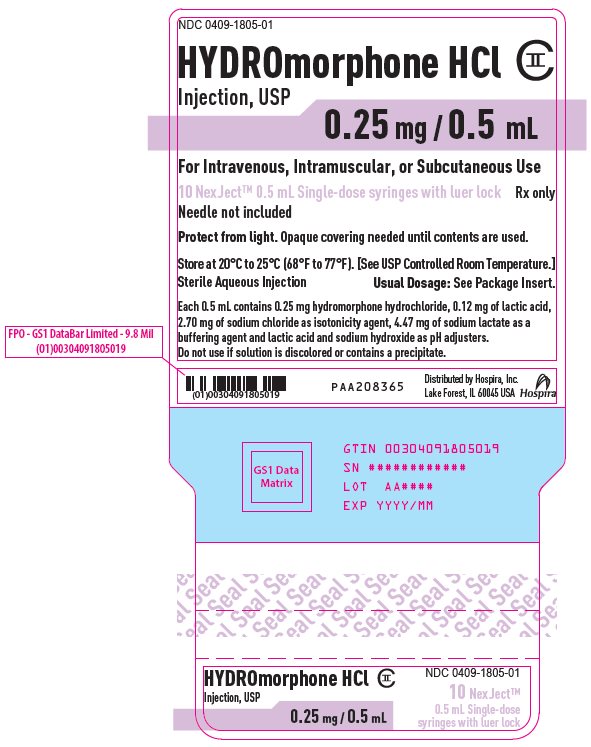 DRUG LABEL: Hydromorphone Hydrochloride
NDC: 0409-1283 | Form: INJECTION, SOLUTION
Manufacturer: Hospira, Inc.
Category: prescription | Type: HUMAN PRESCRIPTION DRUG LABEL
Date: 20260204
DEA Schedule: CII

ACTIVE INGREDIENTS: HYDROMORPHONE HYDROCHLORIDE 1 mg/1 mL
INACTIVE INGREDIENTS: SODIUM LACTATE 8.93 mg/1 mL; SODIUM CHLORIDE 5.40 mg/1 mL; LACTIC ACID, UNSPECIFIED FORM 0.24 mg/1 mL; SODIUM HYDROXIDE

HIGHLIGHTS OF PRESCRIBING INFORMATION

These highlights do not include all the information needed to use HYDROMORPHONE HYDROCHLORIDE INJECTION safely and effectively. See full prescribing information for HYDROMORPHONE HYDROCHLORIDE INJECTION.
HYDROMORPHONE HYDROCHLORIDE injection, for intravenous, intramuscular, or subcutaneous use, CII
Initial U.S. Approval: 1984

RECENT MAJOR CHANGES

Boxed Warning | 12/2025
Indications and Usage (1)‎ | 12/2025
Dosage and Administration (2.6)‎ | 12/2025
Warnings and Precautions (5.1, 5.2, 5.3, 5.10, 5.12) | 12/2025

WARNING: SERIOUS AND LIFE-THREATENING RISKS FROM USE OF ‎HYDROMORPHONE ‎HYDROCHLORIDE INJECTION

See full prescribing information for complete boxed warning.

- Hydromorphone Hydrochloride Injection exposes users to risks of addiction, abuse, and misuse, which can lead to overdose and death. Assess patient's risk before prescribing and reassess regularly for these behaviors and conditions. (5.1).
- Serious, life-threatening, or fatal respiratory depression may occur with use of Hydromorphone Hydrochloride Injection, especially during initiation or following a dosage increase. To reduce the risk of respiratory depression, proper dosing and ‎titration of ‎Hydromorphone Hydrochloride Injection are essential. (5.2).
- Concomitant use of opioids with benzodiazepines or other central nervous system (CNS) depressants, including alcohol, may result in profound sedation, respiratory depression, coma, and death. Reserve concomitant prescribing for use in patients for whom alternative treatment options are inadequate. (5.3, 7).
- Advise pregnant women using opioids for an extended period of time of the risk of Neonatal Opioid Withdrawal Syndrome, which may be life-threatening if not recognized and treated. Ensure that management by neonatology experts will be available at delivery. (5.4).

1 INDICATIONS AND USAGE

Hydromorphone Hydrochloride Injection is an opioid agonist indicated for the management of pain severe enough to require an opioid analgesic and for which alternative treatments are inadequate. (1)
Limitations of Use:

Because of the risks of addiction, abuse, misuse, overdose, and death, which can occur at any dosage or duration and persist over the course of therapy, reserve opioid analgesics, including Hydromorphone Hydrochloride Injection, for use in patients for whom alternative treatment options are ineffective, not tolerated, or would be otherwise inadequate to provide sufficient management of pain. (1, 5.1)

2 DOSAGE AND ADMINISTRATION

- Hydromorphone Hydrochloride Injection should be ‎prescribed only by healthcare professionals who are ‎knowledgeable about the use of opioids ‎and how to ‎mitigate the associated risks. (2.1)‎
- Use the lowest effective dosage for the shortest duration consistent with individual patient treatment goals. Reserve titration to higher doses of Hydromorphone ‎Hydrochloride Injection for ‎patients in whom lower doses are insufficiently ‎effective and in whom the expected benefits of using a higher dose opioid ‎clearly outweigh ‎the substantial risks. (2.1, 5)
- Many acute pain conditions (e.g., the pain that occurs with ‎a number of surgical procedures or acute ‎musculoskeletal injuries) require no more ‎than a few ‎days of an opioid analgesic. Clinical guidelines on ‎opioid prescribing for some acute pain conditions are ‎available. (2.1)
- Initiate the dosing regimen for each patient individually, ‎taking into account the patient’s underlying cause and severity of pain, prior analgesic treatment and response, and risk factors for addiction, abuse, and misuse. (2.1, 5.1)
- Respiratory depression can occur at any time during opioid ‎therapy, especially when initiating and following dosage ‎increases with ‎Hydromorphone Hydrochloride Injection. ‎Consider this risk when selecting an initial dose and when ‎making dose adjustments. (2.1, 5.2)‎
- Intramuscular and Subcutaneous Use: The usual starting dose is 1 mg to 2 mg every 2 to 3 hours as necessary. (2.2)
- Intravenous Use: The usual starting dose is 0.2 mg to 1 mg every 2 to 3 hours. The injection should be given slowly, over at least 2 to 3 minutes. (2.2)
- Hepatic Impairment: Initiate treatment with one-fourth to one-half the usual starting dose, depending on degree of hepatic impairment. (2.3)
- Renal Impairment: Initiate treatment with one-fourth to one-half the usual starting dose, depending on degree of renal impairment. (2.4)
- Periodically reassess patients receiving Hydromorphone Hydrochloride Injection to evaluate the continued need for opioid analgesics to maintain pain control, for the signs or symptoms of adverse reactions, and for the development of addiction, abuse, or misuse. (2.5)
- Do not rapidly reduce or abruptly discontinue Hydromorphone Hydrochloride Injection in a physically-dependent patient. (2.6, 5.12)

3 DOSAGE FORMS AND STRENGTHS

Injection: 0.25 mg/0.5 mL, 0.5 mg/0.5 mL, 1 mg/mL and 2 mg/mL is available in NexJect™ Single-dose Prefilled Syringe with Luer Lock for parenteral administration. (3)

4 CONTRAINDICATIONS

- Significant respiratory depression. (4)
- Acute or severe bronchial asthma in an unmonitored setting or in absence of resuscitative equipment. (4)
- Known or suspected gastrointestinal obstruction, including paralytic ileus. (4)
- Known hypersensitivity to hydromorphone. (4)

5 WARNINGS AND PRECAUTIONS

- Opioid-Induced Hyperalgesia and Allodynia: Opioid-Induced ‎Hyperalgesia (OIH) occurs when an opioid analgesic ‎paradoxically causes an ‎increase in pain, or an increase in ‎sensitivity to pain. If OIH is suspected, carefully consider appropriately ‎‎decreasing the dose of the current opioid analgesic, or ‎opioid rotation. (5.5)‎
- Life-Threatening Respiratory Depression in Patients with Chronic Pulmonary Disease or in Elderly, Cachectic, or Debilitated Patients: Monitor closely, particularly during initiation and titration. (5.6)
- Adrenal Insufficiency: If diagnosed, treat with physiologic replacement of corticosteroids, and wean patient off of the opioid. (5.7)
- Severe Hypotension: Monitor during dosage initiation and titration. Avoid use of Hydromorphone Hydrochloride Injection in patients with circulatory shock. (5.8)
- Risks of Use in Patients with Increased Intracranial Pressure, Brain Tumors, Head Injury, or Impaired Consciousness: Monitor for sedation and respiratory depression. Avoid use of Hydromorphone Hydrochloride Injection in patients with impaired consciousness or coma. (5.9)

6 ADVERSE REACTIONS

Most common adverse reactions are light-headedness, dizziness, sedation, nausea, vomiting, sweating, flushing, dysphoria, euphoria, dry mouth, and pruritus.

Serious adverse reactions include respiratory depression and apnea, circulatory depression, respiratory arrest, shock and cardiac arrest. (6)
To report SUSPECTED ADVERSE REACTIONS, contact Pfizer, Inc. at 1-800-438-1985 or FDA at 1-800-FDA-1088 or www.fda.gov.medwatch.

7 DRUG INTERACTIONS

- Serotonergic Drugs: Concomitant use may result in serotonin syndrome. Discontinue Hydromorphone Hydrochloride Injection if serotonin syndrome is suspected. (7)
- Monoamine Oxidase Inhibitors (MAOIs): Can potentiate the effects of hydromorphone. Avoid concomitant use in patients receiving MAOIs or within 14 days of stopping treatment with an MAOI. (7)
- Mixed Agonist/Antagonist and Partial Agonist Opioid Analgesics: Avoid use with Hydromorphone Hydrochloride Injection because they may reduce analgesic effect of Hydromorphone Hydrochloride Injection or precipitate withdrawal symptoms. (7)

8 USE IN SPECIFIC POPULATIONS

- Pregnancy: May cause fetal harm. (8.1)
- Geriatric Patients: Use caution during dose selection, starting at the low ‎end of the dosing range while carefully monitoring for side effects. ‎‎(8.5)

FULL PRESCRIBING INFORMATION

WARNING: SERIOUS AND LIFE-THREATENING RISKS FROM USE OF ‎HYDROMORPHONE ‎HYDROCHLORIDE INJECTION

Addiction, Abuse, and Misuse

Because use of Hydromorphone Hydrochloride Injection exposes patients and other users to the risks of opioid addiction, abuse, and misuse, which can lead to overdose and death, assess each patient's risk prior to prescribing and reassess all patients regularly for the development of these behaviors and conditions [see Warnings and Precautions (5.1)].

Life-Threatening Respiratory Depression

Serious, life-threatening, or fatal respiratory depression may occur with use of Hydromorphone Hydrochloride Injection, especially during initiation or following a dosage increase. To reduce the risk of respiratory depression, proper dosing and titration of ‎Hydromorphone ‎Hydrochloride Injection are essential [see Warnings and Precautions (5.2)].

Risks From Concomitant Use With Benzodiazepines Or Other CNS Depressants

Concomitant use of opioids with benzodiazepines or other central nervous system (CNS) depressants, including alcohol, may result in profound sedation, respiratory depression, coma, and death. Reserve ‎concomitant prescribing of ‎Hydromorphone Hydrochloride Injection and benzodiazepines or other ‎CNS ‎depressants for use in patients for whom alternative treatment options are ‎inadequate [see Warnings and Precautions (5.3), Drug Interactions (7)].

Neonatal Opioid Withdrawal Syndrome (NOWS)

Advise pregnant women using opioids for an extended period of time of the risk of Neonatal Opioid Withdrawal Syndrome, which may be life-threatening if not recognized and treated. Ensure that management by neonatology experts will be available at delivery [see Warnings and Precautions (5.4)].

1 INDICATIONS AND USAGE

Hydromorphone Hydrochloride Injection is indicated for the management of pain severe enough to require an opioid analgesic and for which alternative treatments are inadequate.

Limitations of Use

Because of the risks of addiction, abuse, misuse, overdose, and death, which can occur at any dosage or duration and persist over the course of therapy [see Warnings and Precautions (5.1)], reserve opioid analgesics, including Hydromorphone Hydrochloride Injection, for use in patients for whom alternative treatment options are ineffective, not tolerated, or would be otherwise inadequate to provide sufficient management of pain.

2 DOSAGE AND ADMINISTRATION

2.1 Important Dosage and Administration Instructions

- Hydromorphone Hydrochloride Injection should be prescribed only by healthcare ‎professionals who are knowledgeable about the use of opioids and how to ‎mitigate the associated risks.
- Use the lowest effective dosage for the shortest duration of time consistent with individual patient treatment goals [see Warnings and Precautions (5)]. Because ‎the risk of overdose increases as opioid doses increase, reserve titration to ‎higher doses of Hydromorphone Hydrochloride Injection for patients in whom ‎lower doses are insufficiently effective and in whom the expected benefits of ‎using a higher dose opioid clearly outweigh the substantial risks.‎
- Many acute pain conditions (e.g., the pain that occurs with a number of surgical ‎procedures or acute musculoskeletal injuries) require no more than a few days ‎of an opioid analgesic. Clinical guidelines on opioid prescribing for some acute ‎pain conditions are available.
- There is variability in the opioid analgesic dose and duration needed to ‎adequately manage pain due both to the cause of pain and to individual patient ‎factors. Initiate the dosing regimen for each patient individually, taking into account the patient’s underlying cause and severity of pain, prior analgesic treatment and response, and risk factors for addiction, abuse, and misuse [see Warnings and Precautions (5.1)].
- Respiratory depression can occur at any time during opioid therapy, especially when initiating and following dosage increases with Hydromorphone Hydrochloride Injection. Consider this risk when selecting an initial dose and ‎when making dose adjustments [see Warnings and Precautions (5)].
- Inspect Hydromorphone Hydrochloride Injection for particulate matter and discoloration prior to administration. A slight yellowish discoloration may develop in Hydromorphone Hydrochloride Injection. No loss of potency has been demonstrated. Hydromorphone Hydrochloride Injection is physically compatible and chemically stable for at least 24 hours at 25°C protected from light in most common large volume parenteral solutions.
- Discard any unused portion in an appropriate manner.

2.2 Initial Dosage

Use of Hydromorphone Hydrochloride Injection as the First Opioid Analgesic

Subcutaneous or Intramuscular Administration

Initiate treatment in a dosing range of 1 mg to 2 mg every 2 to 3 hours as necessary for pain, and at the lowest dose necessary to achieve adequate analgesia. Depending on the clinical situation, the initial starting dose may be lowered in patients who are opioid naïve. Titrate the dose based upon the individual patient’s response to their initial dose ‎of Hydromorphone ‎Hydrochloride Injection.‎

Intravenous Administration

Initiate treatment in a dosing range of 0.2 mg to 1 mg every 2 to 3 hours as necessary for pain control, and at the lowest dose necessary to achieve adequate analgesia. Intravenous administration should be given slowly, over at least 2 to 3 minutes, depending on the dose. Titrate the dose to achieve acceptable pain management and tolerable adverse events. The initial dose should be reduced in the elderly or debilitated and may be lowered to 0.2 mg.

Conversion from Other Opioids to Hydromorphone Hydrochloride Injection

There is inter-patient variability in the potency of opioid drugs and opioid formulations. Therefore, a conservative approach is advised when determining the total daily dosage of Hydromorphone Hydrochloride Injection. It is safer to underestimate a patient's 24-hour Hydromorphone Hydrochloride Injection dosage than to overestimate the 24-hour Hydromorphone Hydrochloride Injection dosage and manage an adverse reaction due to overdose. If the decision is made to convert to Hydromorphone Hydrochloride Injection from another opioid analgesic using publicly available data, convert the current total daily amount(s) of opioid(s) received to an equivalent total daily dose of Hydromorphone Hydrochloride Injection and reduce by one-half due to the possibility of incomplete cross tolerance. Divide the new total amount by the number of doses permitted based on dosing interval (e.g., 8 doses for every-three-hour dosing). Titrate the dose according to the patient's response.

2.3 Dosage Modifications in Patients with Hepatic Impairment

Start patients with hepatic impairment on one-fourth to one-half the usual dose of Hydromorphone Hydrochloride Injection depending on the extent of impairment [see Clinical Pharmacology (12.3)].

2.4 Dosage Modifications in Patients with Renal Impairment

Start patients with renal impairment on one-fourth to one-half the usual starting dose of Hydromorphone Hydrochloride Injection depending on the degree of impairment [see Clinical Pharmacology (12.3)].

2.5 Titration and Maintenance of Therapy

Titrate the dose based upon the individual patient’s response to their initial dose of Hydromorphone Hydrochloride Injection. Individually titrate Hydromorphone Hydrochloride Injection to a dose that provides adequate analgesia and minimizes adverse reactions. Continually reevaluate patients receiving Hydromorphone Hydrochloride Injection to assess the maintenance of pain control, signs and symptoms of opioid withdrawal, and other adverse reactions, as well as to reassess for the development of addiction, abuse, or misuse [see Warnings and Precautions (5.1, 5.12)]. Frequent communication is important among the prescriber, other members of the healthcare team, the patient, and the caregiver/family during periods of changing analgesic requirements, including initial titration.

If the level of pain increases after dosage stabilization, attempt to identify the source of increased pain before increasing the Hydromorphone Hydrochloride Injection dosage. If after increasing the dosage, unacceptable opioid-related adverse reactions are observed (including an increase in pain after a dosage increase), consider reducing the dosage [see Warnings and Precautions (5)]. Adjust the dosage to obtain an appropriate balance between management of pain and opioid-related adverse reactions.

2.6 Safe Reduction and Discontinuation of Hydromorphone Hydrochloride Injection

When a patient who has been taking Hydromorphone Hydrochloride Injection regularly and may be physically dependent no longer requires therapy with Hydromorphone Hydrochloride Injection, taper the dose gradually, by 25% to 50% every 2 to 4 days, while monitoring carefully for signs and symptoms of withdrawal. If the patient develops these signs or symptoms, raise the dose to the previous level and taper more slowly, either by increasing the interval between decreases, decreasing the amount of change in dose, or both. Do not rapidly reduce or abruptly discontinue Hydromorphone Hydrochloride Injection in patients who may be physically dependent on opioids [see Warnings and Precautions (5.12), Drug Abuse and Dependence (9.3)].

3 DOSAGE FORMS AND STRENGTHS

Hydromorphone Hydrochloride Injection, USP is available as:

- Single-dose NexJect™ Syringes | 0.25 mg/0.5 mL, 0.5 mg/0.5 mL, 1 mg/mL and 2 mg/mL

The drug product is a clear, colorless to nearly colorless aqueous sterile solution. Each 1 mL of sterile solution contains 0.5 mg, 1 mg or 2 mg of hydromorphone hydrochloride.

4 CONTRAINDICATIONS

Hydromorphone Hydrochloride Injection is contraindicated in patients with:

- Significant respiratory depression [see Warnings and Precautions (5.2)]
- Acute or severe bronchial asthma in an unmonitored setting or in the absence of resuscitative equipment [see Warnings and Precautions (5.6)]
- Known or suspected gastrointestinal obstruction, including paralytic ileus [see Warnings and Precautions (5.10)]
- Hypersensitivity to hydromorphone (e.g., anaphylaxis) [see Adverse Reactions (6)]

5 WARNINGS AND PRECAUTIONS

5.1 Addiction, Abuse, and Misuse

Hydromorphone Hydrochloride Injection contains hydromorphone, a Schedule II controlled substance. As an opioid, Hydromorphone Hydrochloride Injection exposes users to the risks of addiction, abuse, and misuse [see Drug Abuse and Dependence (9)].

Although the risk of addiction in any individual is unknown, it can occur in patients appropriately prescribed Hydromorphone Hydrochloride Injection. Addiction can occur at recommended dosages and if the drug is misused or abused. The risk of opioid-related overdose or overdose-related death is increased with higher opioid doses, and this risk persists over the course of therapy. In postmarketing studies, addiction, abuse, misuse, and fatal and non-fatal opioid overdose were observed in patients with long-term opioid use [see Adverse Reactions (6)].

Assess each patient's risk for opioid addiction, abuse, or misuse prior to prescribing Hydromorphone Hydrochloride Injection, and monitor all patients receiving Hydromorphone Hydrochloride Injection for the development of these behaviors and conditions. Risks are increased in patients with a personal or family history of substance abuse (including drug or alcohol abuse or addiction) or mental illness (e.g., major depression). The potential for these risks should not, however, prevent the proper management of pain in any given patient. Patients at increased risk may be prescribed opioids such as Hydromorphone Hydrochloride Injection but use in such patients necessitates intensive counseling about the risks and proper use of Hydromorphone Hydrochloride Injection along with intensive monitoring for signs of addiction, abuse, and misuse.

Opioids are sought for nonmedical use and are subject to diversion from ‎legitimate prescribed use. Consider these risks when prescribing or dispensing Hydromorphone Hydrochloride Injection. Strategies to reduce these risks include prescribing the drug in the smallest appropriate quantity. Contact local state professional licensing board or state-controlled substances authority for information on how to prevent and detect abuse or diversion of this product.

5.2 Life-Threatening Respiratory Depression

Serious, life-threatening, or fatal respiratory depression has been reported with the use of opioids, even when used as recommended. Respiratory depression, if not immediately recognized and treated, may lead to respiratory arrest and death. Management of respiratory depression may include close observation, supportive measures, and use of opioid overdose reversal agent (e.g., naloxone, nalmefene), depending on the patient's clinical status [see Overdosage (10)]. Carbon dioxide (CO2) retention from opioid-induced respiratory depression can exacerbate the sedating effects of opioids.

While serious, life-threatening, or fatal respiratory depression can occur at any time during the use of Hydromorphone Hydrochloride Injection, the risk is greatest during the initiation of therapy or following a dosage increase.

To reduce the risk of respiratory depression, proper dosing and titration of Hydromorphone Hydrochloride Injection are essential [see Dosage and Administration (2.1)]. Overestimating the Hydromorphone Hydrochloride Injection dosage when converting patients from another opioid product can result in a fatal overdose with the first dose.

Opioids can cause sleep-related breathing disorders including central sleep apnea (CSA) and sleep-related hypoxemia. Opioid use increases the risk of CSA in a dose-dependent fashion. In patients who present with CSA, consider decreasing the opioid dosage using best practices for opioid taper [see Dosage and Administration (2.1)].

5.3 Risks from Concomitant Use with Benzodiazepines or Other CNS Depressants

Profound sedation, respiratory depression, coma, and death may result from the concomitant use of Hydromorphone Hydrochloride Injection with benzodiazepines and/or other CNS depressants, including alcohol (e.g., non‑benzodiazepine sedatives/hypnotics, anxiolytics, tranquilizers, muscle relaxants, general anesthetics, antipsychotics, gabapentinoids [gabapentin or pregabalin], and other opioids). Because of these risks, reserve concomitant prescribing of these drugs for use in patients for whom alternative treatment options are inadequate.

Observational studies have demonstrated that concomitant use of opioid analgesics and benzodiazepines increases the risk of drug-related mortality compared to use of opioid analgesics alone. Because of similar pharmacological properties, it is reasonable to expect similar risk with the concomitant use of other CNS depressant drugs with opioid analgesics [see Drug Interactions (7)].

If the decision is made to prescribe a benzodiazepine or other CNS depressant concomitantly with an opioid analgesic, prescribe the lowest effective dosages and minimum durations of concomitant use. In patients already receiving an opioid analgesic, prescribe a lower initial dose of the benzodiazepine or other CNS depressant than indicated in the absence of an opioid, and titrate based on clinical response. If an opioid analgesic is initiated in a patient already taking a benzodiazepine or other CNS depressant, prescribe a lower initial dose of the opioid analgesic, and titrate based on clinical response. Monitor patients closely for signs and symptoms of respiratory depression and sedation.

Advise both patients and caregivers about the risks of respiratory depression and sedation when Hydromorphone Hydrochloride Injection is used with benzodiazepines or other CNS depressants (including alcohol and illicit drugs). Advise patients not to drive or operate heavy machinery until the effects of concomitant use of the benzodiazepine or other CNS depressant have been determined. Screen patients for risk of substance use disorders, including opioid abuse and misuse, and warn them of the risk for overdose and death associated with the use of additional CNS depressants including alcohol and illicit drugs [see Drug Interactions (7)].

5.4 Neonatal Opioid Withdrawal Syndrome

Use of Hydromorphone Hydrochloride Injection for an extended period of time during pregnancy can result in withdrawal in the neonate. Neonatal opioid withdrawal syndrome, unlike opioid withdrawal syndrome in adults, may be life-threatening if not recognized and treated, and requires management according to protocols developed by neonatology experts. Observe newborns for signs of neonatal opioid withdrawal syndrome and manage accordingly. Advise pregnant women using opioids for an extended period of time of the risk of neonatal opioid withdrawal syndrome and ensure that management by neonatology experts will be available at delivery [see Use in Specific Populations (8.1)].

5.5 Opioid-Induced Hyperalgesia and Allodynia

Opioid-Induced Hyperalgesia (OIH) occurs when an opioid analgesic ‎paradoxically causes an increase in pain, or an ‎increase in sensitivity to pain. ‎This condition differs from tolerance, which is the need for increasing doses of ‎opioids to ‎maintain a defined effect [Drug Abuse and Dependence (9.3)]. Symptoms of OIH ‎include (but may not be limited to) increased levels ‎of pain upon opioid dosage ‎increase, decreased levels of pain upon opioid dosage decrease, or pain from ‎ordinarily non‑‎painful stimuli (allodynia). These symptoms may suggest OIH only ‎if there is no evidence of underlying disease ‎progression, opioid tolerance, ‎opioid withdrawal, or addictive behavior.‎

Cases of OIH have been reported, both with short-term and longer-term use of ‎opioid analgesics. Though the ‎mechanism of OIH is not fully understood, ‎multiple biochemical pathways have been implicated. Medical literature ‎suggests ‎a strong biologic plausibility between opioid analgesics and OIH and allodynia. If a ‎patient is suspected to be experiencing OIH, ‎carefully consider appropriately ‎decreasing the dose of the current opioid analgesic or opioid rotation (safely ‎switching ‎the patient to a different opioid moiety) [see Dosage and ‎Administration (2.6), Warnings and Precautions (5.12)].‎

5.6 Life-Threatening Respiratory Depression in Patients with Chronic Pulmonary Disease or in Elderly, Cachectic, or Debilitated Patients

The use of Hydromorphone Hydrochloride Injection in patients with acute or severe bronchial asthma in an unmonitored setting or in the absence of resuscitative equipment is contraindicated.

Patients with Chronic Pulmonary Disease: Hydromorphone Hydrochloride Injection-treated patients with significant chronic obstructive pulmonary disease or cor pulmonale, and those with a substantially decreased respiratory reserve, hypoxia, hypercapnia, or pre-existing respiratory depression are at increased risk of decreased respiratory drive including apnea, even at recommended dosages of hydromorphone hydrochloride [see Warnings and Precautions (5.2)].

Elderly, Cachectic, or Debilitated Patients: Life-threatening respiratory depression is more likely to occur in elderly, cachectic, or debilitated patients because they may have altered pharmacokinetics or altered clearance compared to younger, healthier patients [see Warnings and Precautions (5.2)].

Monitor such patients closely, particularly when initiating and titrating Hydromorphone Hydrochloride Injection and when Hydromorphone Hydrochloride Injection is given concomitantly with other drugs that depress respiration [see Warnings and Precautions (5.2, 5.3), Drug Interactions (7)]. Alternatively, consider the use of non-opioid analgesics in these patients.

5.7 Adrenal Insufficiency

Cases of adrenal insufficiency have been reported with opioid use, more often following greater than one month of use. Presentation of adrenal insufficiency may include non-specific symptoms and signs including nausea, vomiting, anorexia, fatigue, weakness, dizziness, and low blood pressure. If adrenal insufficiency is suspected, confirm the diagnosis with diagnostic testing as soon as possible. If adrenal insufficiency is diagnosed, treat with physiologic replacement doses of corticosteroids. Wean the patient off of the opioid to allow adrenal function to recover and continue corticosteroid treatment until adrenal function recovers. Other opioids may be tried as some cases reported use of a different opioid without recurrence of adrenal insufficiency. The information available does not identify any particular opioids as being more likely to be associated with adrenal insufficiency.

5.8 Severe Hypotension

Hydromorphone Hydrochloride Injection may cause severe hypotension including orthostatic hypotension and syncope in ambulatory patients. There is increased risk in patients whose ability to maintain blood pressure has already been compromised by a reduced blood volume or concurrent administration of certain CNS depressant drugs (e.g., phenothiazines or general anesthetics) [see Drug Interactions (7)]. Monitor these patients for signs of hypotension after initiating or titrating the dosage of Hydromorphone Hydrochloride Injection. In patients with circulatory shock, Hydromorphone Hydrochloride Injection may cause vasodilation that can further reduce cardiac output and blood pressure. Avoid the use of Hydromorphone Hydrochloride Injection in patients with circulatory shock.

5.9 Risks of Use in Patients with Increased Intracranial Pressure, Brain Tumors, Head Injury, or Impaired Consciousness

In patients who may be susceptible to the intracranial effects of CO2 retention (e.g., those with evidence of increased intracranial pressure or brain tumors), Hydromorphone Hydrochloride Injection may reduce respiratory drive, and the resultant CO2 retention can further increase intracranial pressure. Monitor such patients for worsening of signs of increasing intracranial pressure. Monitor patients for signs of sedation and respiratory depression, particularly when initiating therapy with Hydromorphone Hydrochloride Injection.

Opioids may also obscure the clinical course in a patient with a head injury. Avoid the use of Hydromorphone Hydrochloride Injection in patients with impaired consciousness or coma.

5.10 Risks of Gastrointestinal Complications

Hydromorphone Hydrochloride Injection is contraindicated in patients with known or suspected gastrointestinal obstruction, including paralytic ileus.

The hydromorphone in Hydromorphone Hydrochloride Injection may cause spasm of the sphincter of Oddi. Opioids may cause increases in serum amylase. Monitor patients with biliary tract disease, including acute pancreatitis, for worsening symptoms.

Cases of opioid-induced esophageal dysfunction (OIED) have been reported in patients taking opioids. The risk of OIED may increase as the dose and/or duration of opioids increases. Regularly evaluate patients for signs and symptoms of OIED (e.g., dysphagia, regurgitation, non-cardiac chest pain) and, if necessary, adjust opioid therapy as clinically appropriate [see Clinical Pharmacology (12.2)].

5.11 Increased Risk of Seizures in Patients with Seizure Disorders

The hydromorphone in Hydromorphone Hydrochloride Injection may increase the frequency of seizures in patients with seizure disorders and may increase the risk of seizures occurring in other clinical settings associated with seizures. Monitor patients with a history of seizure disorders for worsened seizure control during Hydromorphone Hydrochloride Injection therapy.

5.12 Withdrawal

Avoid the use of mixed agonist/antagonist (e.g., pentazocine, nalbuphine, and butorphanol) or partial agonist (e.g., buprenorphine) analgesics in patients who are receiving a full opioid agonist analgesic, including Hydromorphone Hydrochloride Injection. In these patients, mixed agonist/antagonist and partial agonist analgesics may reduce the analgesic effect and/or precipitate withdrawal symptoms [see Drug Interactions (7)].

When discontinuing Hydromorphone Hydrochloride Injection, in a physically-dependent patient, gradually taper the dosage [see Dosage and Administration (2.6)]. Do not rapidly reduce or abruptly discontinue Hydromorphone Hydrochloride Injection in these patients [see Drug Abuse and Dependence (9.3)].

5.13 Risks of Driving and Operating Machinery

Hydromorphone Hydrochloride Injection may impair the mental or physical abilities needed to perform potentially hazardous activities such as driving a car or operating machinery. Warn patients not to drive or operate dangerous machinery unless they are tolerant to the effects of Hydromorphone Hydrochloride Injection and know how they will react to the medication.

5.14 Increased Risk of Hypotension and Respiratory Depression with Rapid Intravenous Administration

Hydromorphone Hydrochloride Injection may be given intravenously, but the injection should be given very slowly. Rapid intravenous injection of opioid analgesics increases the possibility of side effects such as hypotension and respiratory depression [see Dosage and Administration (2.1)].

6 ADVERSE REACTIONS

The following serious adverse reactions are described, or described in greater detail, in other sections:

- Addiction, Abuse, and Misuse [see Warnings and Precautions (5.1)]
- Life-Threatening Respiratory Depression [see Warnings and Precautions (5.2)]
- Interactions with Benzodiazepines or Other CNS Depressants [see Warnings and Precautions (5.3)]
- Neonatal Opioid Withdrawal Syndrome [see Warnings and Precautions (5.4)]
- Opioid-Induced Hyperalgesia and Allodynia [see Warnings and Precautions (5.5)]
- Adrenal Insufficiency [see Warnings and Precautions (5.7)]
- Severe Hypotension [see Warnings and Precautions (5.8)]
- Gastrointestinal Adverse Reactions [see Warnings and Precautions (5.10)]
- Seizures [see Warnings and Precautions (5.11)]
- Withdrawal [see Warnings and Precautions (5.12)]

The following adverse reactions associated with the use of hydromorphone were identified in clinical studies or postmarketing reports. Because some of these reactions were reported voluntarily from a population of uncertain size, it is not always possible to reliably estimate their frequency or establish a causal relationship to drug exposure.

The most common adverse effects are light-headedness, dizziness, sedation, nausea, vomiting, sweating, flushing, dysphoria, euphoria, dry mouth, and pruritus. These effects seem to be more prominent in ambulatory patients and in those not experiencing severe pain.

Less Frequently Observed Adverse Reactions

Cardiac disorders: tachycardia, bradycardia, palpitations

Eye disorders: vision blurred, diplopia, miosis, visual impairment

Gastrointestinal disorders: constipation, ileus, diarrhea, abdominal pain

General disorders and administration site conditions: weakness, feeling abnormal, chills, injection site urticaria

Hepatobiliary disorders: biliary colic

Metabolism and nutrition disorders: decreased appetite

Musculoskeletal and connective tissue disorders: muscle rigidity

Nervous system disorders: headache, tremor, paraesthesia, nystagmus, increased intracranial pressure, syncope, taste alteration, involuntary muscle contractions, presyncope

Psychiatric disorders: agitation, mood altered, nervousness, anxiety, depression, hallucination, disorientation, insomnia, abnormal dreams

Renal and urinary disorders: urinary retention, urinary hesitation, antidiuretic effects

Respiratory, thoracic and mediastinal disorders: bronchospasm, laryngospasm

Skin and subcutaneous tissue disorders: injection site pain, urticaria, rash, hyperhidrosis

Vascular disorders: flushing, hypotension, hypertension

Serotonin syndrome: Cases of serotonin syndrome, a potentially life-threatening condition, have been reported during concomitant use of opioids with serotonergic drugs.

Adrenal insufficiency: Cases of adrenal insufficiency have been reported with opioid use, more often following greater than one month of use.

Anaphylaxis: Anaphylaxis has been reported with ingredients contained in Hydromorphone Hydrochloride Injection.

Androgen deficiency: Cases of androgen deficiency have occurred with use of opioids for an extended period of time.

Hyperalgesia and Allodynia: Cases of hyperalgesia and allodynia have been ‎reported with opioid therapy of ‎any duration. [see Warnings and Precautions ‎‎(5.5)]‎.

Hypoglycemia: Cases of hypoglycemia have been reported in patients ‎taking opioids. Most reports were in ‎patients with at least one ‎predisposing risk factor (e.g., diabetes).‎

Opioid-induced esophageal dysfunction (OIED): Cases of OIED have been reported in patients taking opioids and may occur more frequently in patients taking higher doses of opioids, and/or in patients taking opioids longer term [see Warnings and Precautions (5.10)].

Adverse Reactions from Observational Studies

A prospective, observational cohort study estimated the risks of addiction, abuse, and misuse in patients initiating long-term use of Schedule II opioid analgesics between 2017 and 2021. Study participants included in one or more analyses had been enrolled in selected insurance plans or health systems for at least one year, were free of at least one outcome at baseline, completed a minimum number of follow-up assessments, and either: 1) filled multiple extended-release/long-acting opioid analgesic prescriptions during a 90-day period (n=978); or 2) filled any Schedule II opioid analgesic prescriptions covering at least 70 of 90 days (n=1,244). Those included also had no dispensing of the qualifying opioids in the previous 6 months.

Over 12 months:

- approximately 1% to 6% of participants across the two cohorts newly met criteria for addiction, as assessed with two validated interview-based measures of moderate-to-severe opioid use disorder based on Diagnostic and Statistical Manual of Mental Disorders, Fifth Edition (DSM-5) criteria, and
- approximately 9% and 22% of participants across the two cohorts newly met criteria for prescription opioid abuse and misuse [defined in Drug Abuse and Dependence (9.2)], respectively, as measured with a validated self-reported instrument.

A retrospective, observational cohort study estimated the risk of opioid-involved overdose or opioid overdose‑related death in patients with new long-term use of Schedule II opioid analgesics from 2006 through 2016 (n=220,249). Included patients had been enrolled in either one of two commercial insurance programs, one managed care program, or one Medicaid program for at least 9 months. New long-term use was defined as having Schedule II opioid analgesic prescriptions covering at least 70 days’ supply over the 3 months prior to study entry and none during the preceding 6 months. Patients were excluded if they had an opioid-involved overdose in the 9 months prior to study entry. Overdose was measured using a validated medical code-based algorithm with linkage to the National Death Index database. The 5-year cumulative incidence estimates for opioid-involved overdose or opioid overdose-related death ranged from approximately 1.5% to 4% across study sites, counting only the first event during follow-up. Approximately 17% of first opioid overdoses observed over the entire study period (5-11 years, depending on the study site) were fatal. Higher baseline opioid dose was the strongest and most consistent predictor of opioid-involved overdose or opioid overdose-related death. Study exclusion criteria may have selected patients at lower risk of overdose, and substantial loss to follow-up (approximately 80%) also may have biased estimates.

The risk estimates from the studies described above may not be generalizable to all patients receiving opioid analgesics, such as those with exposures shorter or longer than the duration evaluated in the studies.

7 DRUG INTERACTIONS

Table 1 includes clinically significant drug interactions with Hydromorphone Hydrochloride Injection.

Table 1: Clinically Significant Drug Interactions with Hydromorphone Hydrochloride Injection
Benzodiazepines and other Central Nervous System (CNS) Depressants
Clinical Impact: | Due to additive pharmacologic effect, the concomitant use of benzodiazepines or other CNS depressants, including alcohol, can increase the risk of hypotension, respiratory depression, profound sedation, coma, and death [see Warnings and Precautions (5.3)].
Intervention: | Reserve concomitant prescribing of these drugs for use in patients for whom alternative treatment options are inadequate. Limit dosages and durations to the minimum required. Monitor patients closely for signs of respiratory depression and sedation.
Examples: | Benzodiazepines and other sedatives/hypnotics, anxiolytics, tranquilizers, muscle relaxants, general anesthetics, antipsychotics, gabapentinoids (gabapentin or pregabalin), other opioids, alcohol.
Serotonergic Drugs
Clinical Impact: | The concomitant use of opioids with other drugs that affect the serotonergic neurotransmitter system has resulted in serotonin syndrome.
Intervention: | If concomitant use is warranted, carefully observe the patient, particularly during treatment initiation and dose adjustment. Discontinue Hydromorphone Hydrochloride Injection if serotonin syndrome is suspected.
Examples: | Selective serotonin reuptake inhibitors (SSRIs), serotonin and norepinephrine reuptake inhibitors (SNRIs), tricyclic antidepressants (TCAs), triptans, 5-HT3 receptor antagonists, drugs that effect the serotonin neurotransmitter system (e.g., mirtazapine, trazodone, tramadol), certain muscle relaxants (i.e., cyclobenzaprine, metaxalone), monoamine oxidase (MAO) inhibitors (those intended to treat psychiatric disorders and also others, such as linezolid and intravenous methylene blue).
Monoamine Oxidase Inhibitors (MAOIs)
Clinical Impact: | MAOI interactions with opioids may manifest as serotonin syndrome or opioid toxicity (e.g., respiratory depression, coma) [see Warnings and Precautions (5.2)].
Intervention: | The use of Hydromorphone Hydrochloride Injection is not recommended for patients taking MAOIs or within 14 days of stopping such treatment.; If urgent use of an opioid is necessary, use test doses and frequent titration of small doses to treat pain while closely monitoring blood pressure and signs and symptoms of CNS and respiratory depression.
Examples: | phenelzine, tranylcypromine, linezolid
Mixed Agonist/Antagonist and Partial Agonist Opioid Analgesics
Clinical Impact: | May reduce the analgesic effect of Hydromorphone Hydrochloride Injection and/or precipitate withdrawal symptoms.
Intervention: | Avoid concomitant use.
Examples: | butorphanol, nalbuphine, pentazocine, buprenorphine
Muscle Relaxants
Clinical Impact: | Hydromorphone may enhance the neuromuscular blocking action of skeletal muscle relaxants and produce an increased degree of respiratory depression.
Intervention: | Monitor patients for signs of respiratory depression that may be greater than otherwise expected and decrease the dosage of Hydromorphone Hydrochloride Injection and/or the muscle relaxant as necessary.
Examples: | cyclobenzaprine, metaxalone
Diuretics
Clinical Impact: | Opioids can reduce the efficacy of diuretics by inducing the release of antidiuretic hormone.
Intervention: | Monitor patients for signs of diminished diuresis and/or effects on blood pressure and increase the dosage of the diuretic as needed.
Anticholinergic Drugs
Clinical Impact: | The concomitant use of anticholinergic drugs may increase risk of urinary retention and/or severe constipation, which may lead to paralytic ileus.
Intervention: | Monitor patients for signs of urinary retention or reduced gastric motility when Hydromorphone Hydrochloride Injection is used concomitantly with anticholinergic drugs.

8 USE IN SPECIFIC POPULATIONS

8.1 Pregnancy

Risk Summary

Use of opioid analgesics for an extended period of time during pregnancy may cause neonatal opioid withdrawal syndrome [see Warnings and Precautions (5.4)]. There are no available data with Hydromorphone Hydrochloride Injection in pregnant women to inform a drug-associated risk for major birth defects and miscarriage or adverse maternal outcomes‎.‎ There are adverse outcomes reported with fetal exposure to opioid analgesics [see Clinical Considerations].

In published animal reproduction studies, neural tube defects were noted following subcutaneous injection of hydromorphone to pregnant hamsters at doses 6.4 times the HDD and soft tissue and skeletal abnormalities were noted following subcutaneous continuous infusion of 3 times the HDD to pregnant mice. No malformations were noted at 4 or 40.5 times the HDD in pregnant rats or rabbits, respectively [see Data]. Based on animal data, advise pregnant women of the potential risk to a fetus.

The background risk of major birth defects and miscarriage for the indicated population is unknown. All pregnancies have a background risk of birth defect, loss, or other adverse outcomes. In the U.S. general population, the estimated background risk of major birth defects and miscarriage in clinically recognized pregnancies is 2 to 4% and 15 to 20%, respectively.

Clinical Considerations

Fetal/Neonatal Adverse Reactions

Use of opioid analgesics for an extended period of time during pregnancy for medical or nonmedical purposes can result in physical dependence in the neonate and neonatal opioid withdrawal syndrome shortly after birth.

Neonatal opioid withdrawal syndrome presents as irritability, hyperactivity and abnormal sleep pattern, high pitched cry, tremor, vomiting, diarrhea, and failure to gain weight. The onset, duration, and severity of neonatal opioid withdrawal syndrome vary based on the specific opioid used, duration of use, timing and amount of last maternal use, and rate of elimination of the drug by the newborn. Observe newborns for symptoms of neonatal opioid withdrawal syndrome and manage accordingly [see Warnings and Precautions (5.4)].

Labor or Delivery

Opioids cross the placenta and may produce respiratory depression and psycho-physiologic effects in neonates. An opioid overdose reversal agent, such as naloxone or nalmefene, must be available for reversal of opioid‑induced respiratory depression in the neonate. Hydromorphone Hydrochloride Injection is not recommended for use in pregnant women during or immediately prior to labor, when other analgesic techniques are more appropriate. Opioid analgesics, including Hydromorphone Hydrochloride Injection, can prolong labor through actions which temporarily reduce the strength, duration, and frequency of uterine contractions. However, this effect is not consistent and may be offset by an increased rate of cervical dilation, which tends to shorten labor. Monitor neonates exposed to opioid analgesics during labor for signs of excess sedation and respiratory depression.

Data

Animal Data

No effects on teratogenicity or embryotoxicity were observed in pregnant rats given oral doses up to 7 mg/kg/day which is 3-fold higher than the human dose of 24 mg Hydromorphone Hydrochloride Injection (4 mg every 4 hours), on a body surface area basis.

In a published study, neural tube defects (exencephaly and cranioschisis) were noted following subcutaneous administration of hydromorphone hydrochloride (19 to 258 mg/kg) on Gestation Day 8 to pregnant hamsters (6.4 to 87.2 times the HDD of 24 mg/day based on body surface area). The findings cannot be clearly attributed to maternal toxicity. No neural tube defects were noted at 14 mg/kg (4.7 times the human daily dose of 24 mg/day).

In a published study, CF-1 mice were treated subcutaneously with continuous infusion of 7.5, 15, or 30 mg/kg/day hydromorphone hydrochloride (1.5, 3, or 6.1 times the human daily dose of 24 mg based on body surface area) via implanted osmotic pumps during organogenesis (Gestation Days 7 to 10). Soft tissue malformations (cryptorchidism, cleft palate, malformed ventricles and retina), and skeletal variations (split supraoccipital, checkerboard and split sternebrae, delayed ossification of the paws and ectopic ossification sites) were observed at doses 3 times the human dose of 24 mg/day based on body surface area. The findings cannot be clearly attributed to maternal toxicity.

8.2 Lactation

Risk Summary

Low levels of opioid analgesics have been detected in human milk. The developmental and health benefits of breastfeeding should be considered along with the mother's clinical need for Hydromorphone Hydrochloride Injection and any potential adverse effects on the breastfed infant from Hydromorphone Hydrochloride Injection or from the underlying maternal condition.

Clinical Considerations

Monitor infants exposed to hydromorphone hydrochloride through breast milk for excess sedation and respiratory depression. Withdrawal symptoms can occur in breastfed infants when maternal administration of hydromorphone is stopped, or when breast-feeding is stopped.

8.3 Females and Males of Reproductive Potential

Infertility

Use of opioids for an extended period of time may cause reduced fertility in females and males of reproductive potential. It is not known whether these effects on fertility are reversible [see Adverse Reactions (6), Clinical Pharmacology (12.2)].

8.4 Pediatric Use

The safety and effectiveness of Hydromorphone Hydrochloride Injection in pediatric patients has not been established.

8.5 Geriatric Use

Elderly patients (aged 65 years or older) may have increased sensitivity to hydromorphone. In general, use caution when selecting a dosage for an elderly patient, usually starting at the low end of the dosing range, reflecting the greater frequency of decreased hepatic, renal, or cardiac function and of concomitant disease or other drug therapy.

Respiratory depression is the chief risk for elderly patients treated with opioids and has occurred after large initial doses were administered to patients who were not opioid-tolerant or when opioids were co-administered with other agents that depress respiration. Titrate the dosage of Hydromorphone Hydrochloride Injection slowly in geriatric patients and monitor closely for signs of central nervous system and respiratory depression [see Warnings and Precautions (5.6)].

Hydromorphone is known to be substantially excreted by the kidney, and the risk of adverse reactions to this drug may be greater in patients with impaired renal function. Because elderly patients are more likely to have decreased renal function, care should be taken in dose selection, and it may be useful to monitor renal function.

8.6 Hepatic Impairment

The pharmacokinetics of hydromorphone are affected by hepatic impairment. Due to increased exposure of hydromorphone, patients with moderate hepatic impairment should be started at one fourth to one half the recommended starting dose depending on the degree of hepatic dysfunction and closely monitored during dose titration. The pharmacokinetics of hydromorphone in patients with severe hepatic impairment has not been studied. A further increase in Cmax and AUC of hydromorphone in this group is expected and should be taken into consideration when selecting a starting dose [see Clinical Pharmacology (12.3)].

8.7 Renal Impairment

The pharmacokinetics of hydromorphone are affected by renal impairment. In addition, in patients with severe renal impairment, hydromorphone appeared to be more slowly eliminated with a longer terminal elimination half-life. Start patients with renal impairment on one-fourth to one-half the usual starting dose depending on the degree of impairment. Patients with renal impairment should be closely monitored during dose titration [see Clinical Pharmacology (12.3)].

9 DRUG ABUSE AND DEPENDENCE

9.1 Controlled Substance

Hydromorphone Hydrochloride Injection contains hydromorphone, a Schedule II controlled substance.

9.2 Abuse

Hydromorphone Hydrochloride Injection contains hydromorphone, a substance with high potential for misuse and abuse, which can lead to the development of ‎substance use disorder, including addiction [see Warnings and Precautions (5.1)].

Misuse is the intentional use, for therapeutic purposes, of a drug by an ‎individual in a way other than ‎‎prescribed by a healthcare provider or for ‎whom it was not prescribed.‎

Abuse is the intentional non-therapeutic use of a drug, even once, for its desirable psychological or physiological effects.

Drug addiction is a cluster of behavioral, cognitive, and physiological phenomena that may include a strong desire to take the drug, difficulties in controlling drug use (e.g., continuing drug, use despite harmful consequences, giving a higher priority to drug use than other activities and obligations), and possible tolerance or physical dependence.

Misuse and abuse of Hydromorphone Hydrochloride Injection increases ‎risk of overdose, which may lead to ‎central nervous system and ‎respiratory depression, hypotension, seizures, and death. The risk is ‎increased with ‎concurrent abuse of Hydromorphone Hydrochloride ‎Injection with alcohol and/or other CNS ‎depressants.‎ Abuse of and addiction to opioids in some individuals may not be ‎accompanied by concurrent ‎tolerance and symptoms of physical ‎dependence. In addition, abuse of opioids can occur in the absence of ‎‎addiction.‎

All patients treated with opioids require careful and frequent reevaluation ‎for signs of misuse, abuse, and ‎addiction, because use of opioid analgesic ‎products carries the risk of addiction even under appropriate ‎medical use. ‎Patients at high risk of Hydromorphone Hydrochloride Injection abuse ‎include those with a ‎history of prolonged use of any opioid, including products containing ‎hydromorphone, those with a history of drug or alcohol abuse, ‎or those ‎who use Hydromorphone Hydrochloride Injection in combination with ‎other abused drugs.‎

"Drug-seeking" behavior is very common in persons with substance use disorders. Drug-seeking tactics include emergency calls or visits near the end of office hours, refusal to undergo appropriate examination, testing, or referral, repeated "loss" of prescriptions, tampering with prescriptions and reluctance to provide prior medical records or contact information for other treating health care provider(s). "Doctor shopping" (visiting multiple prescribers to obtain additional prescriptions) is common among people who abuse drugs and people with substance use disorder. Preoccupation with achieving adequate pain relief can be appropriate behavior in a patient with inadequate pain control.

Hydromorphone Hydrochloride Injection, like other opioids, can be diverted for nonmedical use into illicit channels of distribution. Careful record-keeping of prescribing information, including quantity, frequency, and renewal requests, as required by state and federal law, is strongly advised.

Proper assessment of the patient, proper prescribing practices, periodic reevaluation of therapy, and proper dispensing and storage are appropriate measures that help to limit abuse of opioid drugs.

Risks Specific to Abuse of Hydromorphone Hydrochloride Injection

Abuse of Hydromorphone Hydrochloride Injection poses a risk of overdose and death. The risk is increased with concurrent use of Hydromorphone Hydrochloride Injection with alcohol and/or other CNS depressants.

Parenteral drug abuse is commonly associated with transmission of infectious diseases such as hepatitis and HIV.

9.3 Dependence

Both tolerance and physical dependence can develop during use of opioid therapy.

Tolerance is a physiological state characterized by a reduced response to ‎a drug after repeated administration (i.e., a ‎higher ‎dose of a drug is ‎required to produce the same effect that was once obtained at a lower ‎dose).‎

Physical dependence is a state that develops as a result of a physiological ‎adaptation in response to repeated drug use, ‎manifested ‎by withdrawal signs and symptoms after abrupt discontinuation or a significant dose reduction of a drug.

Withdrawal may be precipitated through the administration of drugs with opioid antagonist activity (e.g., naloxone, nalmefene), mixed agonist/antagonist analgesics (e.g., pentazocine, butorphanol, nalbuphine), or partial agonists (e.g., buprenorphine). Physical dependence may not occur to a clinically significant degree until after several days to weeks of continued use.

Hydromorphone Hydrochloride Injection should not be rapidly reduced or abruptly discontinued in a physically-dependent patient [see Dosage and Administration (2.6)]. If Hydromorphone Hydrochloride Injection is rapidly reduced or abruptly discontinued in a physically-dependent patient, a withdrawal syndrome may occur, typically ‎characterized by restlessness, lacrimation, rhinorrhea, perspiration, chills, myalgia, and mydriasis. Other signs and symptoms also may develop, including irritability, anxiety, backache, joint pain, weakness, abdominal cramps, insomnia, nausea, anorexia, vomiting, diarrhea, or increased blood pressure, respiratory rate, or heart rate.

Infants born to mothers physically-dependent on opioids will also be physically-dependent and may exhibit respiratory difficulties and withdrawal signs [see Use in Specific Populations (8.1)].

10 OVERDOSAGE

Clinical Presentation

Acute overdose with hydromorphone can be manifested by respiratory depression, somnolence progressing to stupor or coma, skeletal muscle flaccidity, cold and clammy skin, constricted pupils, and, in some cases, pulmonary edema, bradycardia, hypotension, hypoglycemia, partial or complete airway obstruction, atypical snoring, and death. Marked mydriasis rather than miosis may be seen with hypoxia in overdose situations [see Clinical Pharmacology (12.2)]. Toxic leukoencephalopathy has been reported after opioid overdose and can present hours, days, or weeks after apparent recovery from the initial intoxication.

Treatment of Overdose

In case of overdose, priorities are the reestablishment of a patent and protected airway and institution of assisted or controlled ventilation, if needed. Employ other supportive measures (including oxygen and vasopressors) in the management of circulatory shock and pulmonary edema as indicated. Cardiac arrest or arrhythmias will require advanced life-support measures.

For clinically significant respiratory or circulatory depression secondary to hydromorphone overdose, administer an opioid overdose reversal agent such as naloxone or nalmefene.

Because the duration of opioid reversal is expected to be less than the duration of action of hydromorphone in Hydromorphone Hydrochloride Injection, carefully monitor the patient until spontaneous respiration is reliably reestablished. If the response to an opioid overdose reversal agent is suboptimal or only brief in nature, administer additional reversal agent as directed by the product's prescribing information.

In an individual physically-dependent on opioids, administration of the recommended usual dosage of the opioid overdose reversal agent will precipitate an acute withdrawal syndrome. The severity of the withdrawal symptoms experienced will depend on the degree of physical dependence and the dose of the reversal agent administered. If a decision is made to treat serious respiratory depression in the physically-dependent patient, administration of the reversal agent should be initiated with care and by titration with smaller than usual doses of the reversal agent.

11 DESCRIPTION

Hydromorphone Hydrochloride Injection is available as an aqueous sterile solution, for use in intravenous, intramuscular and subcutaneous administration, and contains hydromorphone as active pharmaceutical ingredient in the form hydrochloride salt. Hydromorphone hydrochloride is an opioid agonist.

The chemical name of hydromorphone hydrochloride is 4,5α- epoxy-3-hydroxy-17-methylmorphinan-6-one hydrochloride. The molecular weight is 321.8 and it has the following chemical structure.

Hydromorphone hydrochloride is a white or almost white crystalline powder that is freely soluble in water, very slightly soluble in ethanol (96%), and practically insoluble in methylene chloride.

Each mL of Hydromorphone Hydrochloride Injection sterile solution contains 0.5 mg, 1 mg or 2 mg of Hydromorphone Hydrochloride USP, equivalent to 0.44 mg, 0.89 mg or 1.77 mg of hydromorphone free base, respectively, 0.24 mg of Lactic Acid USP, 5.40 mg of Sodium Chloride as isotonicity agent, 8.93 mg of Sodium Lactate USP as buffering agent, and Lactic Acid USP and Sodium Hydroxide NF as pH adjusters, in Water for Injection. Hydromorphone Hydrochloride Injection pH range is 3.5 to 5.5.

12 CLINICAL PHARMACOLOGY

12.1 Mechanism of Action

Hydromorphone is a full opioid agonist and is relatively selective for the mµ-opioid receptor, although it can bind to other opioid receptors at higher doses. The principal therapeutic action of hydromorphone is analgesia. Like all full opioid agonists, there is no ceiling effect for analgesia with morphine. Clinically, dosage is titrated to provide adequate analgesia and may be limited by adverse reactions, including respiratory and CNS depression.

The precise mechanism of the analgesic action is unknown. However, specific CNS opioid receptors for endogenous compounds with opioid-like activity have been identified throughout the brain and spinal cord and are thought to play a role in the analgesic effects of this drug.

12.2 Pharmacodynamics

Effects on the Central Nervous System

Hydromorphone produces respiratory depression by direct action on brain stem respiratory centers. The respiratory depression involves a reduction in the responsiveness of the brain stem respiratory centers to both increases in carbon dioxide tension and electrical stimulation.

Hydromorphone causes miosis, even in total darkness. Pinpoint pupils are a sign of opioid overdose but are not pathognomonic (e.g., pontine lesions of hemorrhagic or ischemic origins may produce similar findings). Marked mydriasis rather than miosis may be seen due to hypoxia in overdose situations.

Effects on the Gastrointestinal Tract and Other Smooth Muscle

Hydromorphone causes a reduction in motility associated with an increase in smooth muscle tone in the antrum of the stomach and duodenum. Digestion of food in the small intestine is delayed and propulsive contractions are decreased. Propulsive peristaltic waves in the colon are decreased, while tone may be increased to the point of spasm resulting in constipation. Other opioid-induced effects may include a reduction in biliary and pancreatic secretions, spasm of sphincter of Oddi, transient elevations in serum amylase, and opioid-induced esophageal dysfunction (OIED).

Effects on the Cardiovascular System

Hydromorphone produces peripheral vasodilation which may result in orthostatic hypotension or syncope. Manifestations of histamine release and/or peripheral vasodilation may include pruritus, flushing, red eyes and sweating and/or orthostatic hypotension.

Effects on the Endocrine System

Opioids inhibit the secretion of adrenocorticotropic hormone (ACTH), cortisol, and luteinizing hormone (LH) in humans [see Adverse Reactions (6)]. They also stimulate prolactin, growth hormone (GH) secretion, and pancreatic secretion of insulin and glucagon [see Adverse Reactions (6)].

Use of opioids for an extended period of time may influence the hypothalamic-pituitary-gonadal axis, leading to androgen deficiency that may manifest as low libido, impotence, erectile dysfunction, amenorrhea, or infertility. The causal role of opioids in the clinical syndrome of hypogonadism is unknown because the various medical, physical, lifestyle, and psychological stressors that may influence gonadal hormone levels have not been adequately controlled for in studies conducted to date [see Adverse Reactions (6)].

Effects on the Immune System

Opioids have been shown to have a variety of effects on components of the immune system in in vitro and animal models. The clinical significance of these findings is unknown. Overall, the effects of opioids appear to be modestly immunosuppressive.

Concentration–Efficacy Relationships

The minimum effective analgesic concentration will vary widely among patients, especially among patients who have been previously treated with opioid agonists. The minimum effective analgesic concentration of hydromorphone for any individual patient may increase over time due to an increase in pain, the development of a new pain syndrome and/or the development of analgesic tolerance [see Dosage and Administration (2.1, 2.5)].

Concentration–Adverse Reaction Relationships

There is a relationship between increasing hydromorphone plasma concentration and increasing frequency of dose-related opioid adverse reactions such as nausea, vomiting, CNS effects, and respiratory depression. In opioid-tolerant patients, the situation may be altered by the development of tolerance to opioid-related adverse reactions [see Dosage and Administration (2.1, 2.5)].

12.3 Pharmacokinetics

Distribution

At therapeutic plasma levels, hydromorphone is approximately 8–19% bound to plasma proteins. After an intravenous bolus dose, the steady state of volume of distribution [mean (%CV)] is 302.9 (32%) liters.

Elimination

The systemic clearance is approximately 1.96 (20%) liters/minute. The terminal elimination half-life of hydromorphone after an intravenous dose is about 2.3 hours.

Metabolism

Hydromorphone is extensively metabolized via glucuronidation in the liver, with greater than 95% of the dose metabolized to hydromorphone-3-glucuronide along with minor amounts of 6-hydroxy reduction metabolites.

Excretion

Only a small amount of the hydromorphone dose is excreted unchanged in the urine. Most of the dose is excreted as hydromorphone-3-glucuronide along with minor amounts of 6-hydroxy reduction metabolites.

Specific Populations

Hepatic Impairment

After oral administration of hydromorphone at a single 4 mg dose (2 mg hydromorphone immediate-release tablets), mean exposure to hydromorphone (Cmax and AUC∞) is increased 4-fold in patients with moderate (Child-Pugh Group B) hepatic impairment compared with subjects with normal hepatic function. Patients with moderate hepatic impairment should be started at one fourth to one half the recommended starting dose and closely monitored during dose titration. The pharmacokinetics of hydromorphone in patients with severe hepatic impairment has not been studied. A further increase in Cmax and AUC of hydromorphone in this group is expected and should be taken into consideration when selecting a starting dose [see Use in Specific Populations (8.6)].

Renal Impairment

The pharmacokinetics of hydromorphone following an oral administration of hydromorphone at a single 4 mg dose (2 mg hydromorphone immediate-release tablets) are affected by renal impairment. Mean exposure to hydromorphone (Cmax and AUC0–∞) is increased by 2-fold in patients with moderate (CLcr = 40 – 60 mL/min) renal impairment and increased by 4-fold in patients with severe (CLcr < 30 mL/min) renal impairment compared with normal subjects (CLcr > 80 mL/min). In addition, in patients with severe renal impairment, hydromorphone appeared to be more slowly eliminated with a longer terminal elimination half-life (40 hr) compared to patients with normal renal function (15 hr). Start patients with renal impairment on one-fourth to one-half the usual starting dose depending on the degree of impairment. Patients with renal impairment should be closely monitored during dose titration [see Use in Specific Populations (8.7)].

Age: Geriatric Population

In the geriatric population, age has no effect on the pharmacokinetics of hydromorphone.

Sex

Sex has little effect on the pharmacokinetics of hydromorphone. Females appear to have a higher Cmax (25%) than males with comparable AUC0–24 values. The difference observed in Cmax may not be clinically relevant.

13 NONCLINICAL TOXICOLOGY

13.1 Carcinogenesis, Mutagenesis, Impairment of Fertility

Carcinogenesis

Long-term studies in animals to evaluate the carcinogenic potential of hydromorphone have not been conducted.

Mutagenesis

Hydromorphone was not mutagenic in the in vitro bacterial reverse mutation assay (Ames assay). Hydromorphone was not clastogenic in either the in vitro human lymphocyte chromosome aberration assay or the in vivo mouse micronucleus assay.

Impairment of Fertility

No effects on fertility, reproductive performance, or reproductive organ morphology were observed in male or female rats given oral doses up to 7 mg/kg/day which is 2.8 times the human dose of 24 mg hydromorphone hydrochloride injection (4 mg every 4 hours), on a body surface area basis.

16 HOW SUPPLIED/STORAGE AND HANDLING

Safety and Handling Instructions

Access to drugs with a potential for abuse such as Hydromorphone Hydrochloride Injection presents an occupational hazard for addiction in the health care industry. Routine procedures for handling controlled substances developed to protect the public may not be adequate to protect health care workers. Implementation of more effective accounting procedures and measures to restrict access to drugs of this class (appropriate to the practice setting) may minimize the risk of self-administration by health care providers.

How Supplied

Hydromorphone Hydrochloride Injection is supplied as a sterile solution in single‑dose NexJectTM prefilled syringes for intravenous, intramuscular, and subcutaneous administration, and available as follows:

Unit of Sale | Concentration (per total volume)
NDC 0409-1805-01; Clamshell of 10; 0.5 mL fill in 1.5 mL NexJect™ Single-dose Prefilled Syringe with Luer Lock | 0.25 mg/0.5 mL
NDC 0409-4264-01 Clamshell of 10 0.5 mL fill in 1.5 mL NexJect™ Single-dose Prefilled Syringe with Luer Lock | 0.5 mg/0.5 mL
NDC 0409-1283-37 Clamshell of 10 1 mL fill in 1.5 mL NexJect™ Single-dose Prefilled Syringe with Luer Lock | 1 mg/mL
NDC 0409-1312-36 Clamshell of 10 1 mL fill in 1.5 mL NexJect™ Single-dose Prefilled Syringe with Luer Lock | 2 mg/mL

STORAGE AND HANDLING

Note that a needle is not included.

PROTECT FROM LIGHT

Keep covered in carton until time of use. Store at 20°C to 25°C (68°F to 77°F); excursions permitted to 15°C to 30°C (59°F to 86°F) [See USP Controlled Room Temperature].

17 PATIENT COUNSELING INFORMATION

Addiction, Abuse, and Misuse

Inform patients that the use of Hydromorphone Hydrochloride Injection, even when taken as recommended, can result in addiction, abuse, and misuse, which can lead to overdose and death [see Warnings and Precautions (5.1)]. Instruct patients not to share Hydromorphone Hydrochloride Injection with others and to take steps to protect Hydromorphone Hydrochloride Injection from theft or misuse.

Life-Threatening Respiratory Depression

Inform patients of the risk of life-threatening respiratory depression, including information that the risk is greatest when starting Hydromorphone Hydrochloride Injection or when the dosage is increased, and that it can occur even at recommended dosages ‎[see Warnings and Precautions (5.2)]‎.

Hyperalgesia and Allodynia

Advise ‎patients to inform their healthcare provider if they ‎experience symptoms of hyperalgesia, including worsening pain, ‎increased ‎sensitivity to pain, or new pain [see Warnings and Precautions (5.5), ‎Adverse Reactions (6)].‎

Serotonin Syndrome

Inform patients that opioids could cause a rare but potentially life-threatening condition called serotonin syndrome resulting from concomitant administration of serotonergic drugs. Warn patients of the symptoms of serotonin syndrome and to seek medical attention right away if symptoms develop after discharge from the hospital. Instruct patients to inform their physicians if they are taking, or plan to take serotonergic medications [see Drug Interactions (7)].

Constipation

Advise patients of the potential for severe constipation, including management instructions and when to seek medical attention [see Adverse Reactions (6)].

Distributed by Hospira, Inc., Lake Forest, IL 60045 USA

LAB-0980-6.0

INSTRUCTIONS FOR USE

Parenteral drug products should be inspected visually for particulate matter and discoloration prior to ‎‎‎administration, whenever solution and container permit. Do not use if color is darker than pale yellow, if it ‎‎is ‎discolored in any other way, or if it contains a precipitate.‎

NexJect™ Single-dose Prefilled Syringe

Instructions for use – NexJect Prefilled Syringe

NOTE: To prevent needlestick injuries, do not recap, purposely bend, or break by hand used ‎needles. Do not recap, purposely bend, or break by ‎hand blunt Cannulas.

Distributed by Hospira, Inc., Lake Forest, IL 60045 USA

LAB-1382-3.0

Revised: 12/2023

PRINCIPAL DISPLAY PANEL - 1 mg/mL Syringe Label

HYDROmorphone HCl
Injection, USP

PAA140442

CII

1 mg/mL

PRINCIPAL DISPLAY PANEL - 1 mg/mL Syringe Label - 1283

TWIST & PULL

Tamper Seal

NDC 0409-1283-17

CII

HYDROmorphone HCl
Injection, USP

1 mg/mL

Intravenous, Intramuscular,
or Subcutaneous Use

Protect from light
Rx only

1 mL Single-dose syringe

PAA140444

LOT #####AA
EXP DMMMYYYY

PRINCIPAL DISPLAY PANEL - 1 mg/mL Syringe Cello Pack Label

NDC 0409-1283-37

HYDROmorphone HCl
Injection, USP

CII

1 mg / mL

For Intravenous, Intramuscular, or Subcutaneous Use

10 NexJect™ 1 mL Single-dose syringes with luer lock
Rx only

Needle not included

Protect from light. Opaque covering needed until contents are used.

Store at 20°C to 25°C (68°F to 77°F). [See USP Controlled Room Temperature.]

Sterile Aqueous Injection
Usual Dosage: See Package Insert.

Each mL contains 1 mg hydromorphone hydrochloride, 0.24 mg of lactic acid,
5.40 mg sodium chloride as isotonicity agent, 8.93 mg of sodium lactate as a
buffering agent and lactic acid and sodium hydroxide as pH adjusters.

Do not use if solution is discolored or contains a precipitate.

PAA211792

Distributed by Hospira, Inc.
Lake Forest, IL 60045 USA

Hospira

PRINCIPAL DISPLAY PANEL - 2 mg/mL Syringe Label

HYDROmorphone HCl
Injection, USP

PAA140441

CII

2 mg/mL

PRINCIPAL DISPLAY PANEL - 2 mg/mL Syringe Label - 1312

TWIST & PULL

Tamper Seal

NDC 0409-1312-16

CII

HYDROmorphone HCl
Injection, USP

2 mg/mL

Intravenous, Intramuscular,
or Subcutaneous Use

Protect from light
Rx only

1 mL Single-dose syringe

PAA140445

LOT #####AA
EXP DMMMYYYY

PRINCIPAL DISPLAY PANEL - 2 mg/mL Syringe Cello Pack Label

NDC 0409-1312-36

HYDROmorphone HCl
Injection, USP

CII

2 mg / mL

For Intravenous, Intramuscular, or Subcutaneous Use

10 NexJect™ 1 mL Single-dose syringes with luer lock
Rx only

Needle not included

Protect from light. Opaque covering needed until contents are used.

Store at 20°C to 25°C (68°F to 77°F). [See USP Controlled Room Temperature.]

Sterile Aqueous Injection
Usual Dosage: See Package Insert.

Each mL contains 2 mg hydromorphone hydrochloride, 0.24 mg of lactic acid,
5.40 mg sodium chloride as isotonicity agent, 8.93 mg of sodium lactate as a
buffering agent and lactic acid and sodium hydroxide as pH adjusters.

Do not use if solution is discolored or contains a precipitate.

PAA211791

Distributed by Hospira, Inc.
Lake Forest, IL 60045 USA

Hospira

PRINCIPAL DISPLAY PANEL - 0.5 mg/0.5 mL Syringe Label

HYDROmorphone HCl
Injection, USP

PAA152907

CII

0.5 mg/0.5 mL

PRINCIPAL DISPLAY PANEL - 0.5 mg/0.5 mL Syringe Label - 4264

TWIST & PULL

Tamper Seal

NDC 0409-4264-11

CII

HYDROmorphone HCl
Injection, USP

0.5 mg/0.5 mL

Intravenous, Intramuscular,
or Subcutaneous Use

Protect from light
Rx only

0.5 mL Single-dose syringe

PAA152909

LOT #####AA
EXP DMMMYYYY

PRINCIPAL DISPLAY PANEL - 0.5 mg/0.5 mL Syringe Cello Pack Label

NDC 0409-4264-01

HYDROmorphone HCl
Injection, USP

CII

0.5 mg / 0.5 mL

For Intravenous, Intramuscular, or Subcutaneous Use

10 NexJect™ 0.5 mL Single-dose syringes with luer lock
Rx only

Needle not included

Protect from light. Opaque covering needed until contents are used.

Store at 20°C to 25°C (68°F to 77°F). [See USP Controlled Room Temperature.]

Sterile Aqueous Injection
Usual Dosage: See Package Insert.

Each 0.5 mL contains 0.5 mg hydromorphone hydrochloride, 0.12 mg of lactic acid,
2.70 mg sodium chloride as isotonicity agent, 4.47 mg of sodium lactate as a
buffering agent and lactic acid and sodium hydroxide as pH adjusters.

Do not use if solution is discolored or contains a precipitate.

PAA211659

Distributed by Hospira, Inc.
Lake Forest, IL 60045 USA

Hospira

PRINCIPAL DISPLAY PANEL - 0.25 mg/0.5 mL Syringe Label

HYDROmorphone HCl
Injection, USP

PAA208366

CII

0.25 mg/0.5 mL

PRINCIPAL DISPLAY PANEL - 0.25 mg/0.5 mL Syringe Label - 1805

TWIST & PULL

Tamper Seal

NDC 0409-1805-10

CII

HYDROmorphone HCl
Injection, USP

0.25 mg/0.5 mL

Intravenous, Intramuscular,
or Subcutaneous Use

Protect from light
Rx only

0.5 mL Single-dose syringe

PAA208364

LOT AA####
EXP YYYY / MM

PRINCIPAL DISPLAY PANEL - 0.25 mg/0.5 mL Syringe Cello Pack Label

NDC 0409-1805-01

HYDROmorphone HCl
Injection, USP
CII

0.25 mg / 0.5 mL

For Intravenous, Intramuscular, or Subcutaneous Use

10 NexJect™ 0.5 mL Single-dose syringes with luer lock
Rx only

Needle not included

Protect from light. Opaque covering needed until contents are used.

Store at 20°C to 25°C (68°F to 77°F). [See USP Controlled Room Temperature.]

Sterile Aqueous Injection
Usual Dosage: See Package Insert.

Each 0.5 mL contains 0.25 mg hydromorphone hydrochloride, 0.12 mg of lactic acid,
2.70 mg of sodium chloride as isotonicity agent, 4.47 mg of sodium lactate as a
buffering agent and lactic acid and sodium hydroxide as pH adjusters.
Do not use if solution is discolored or contains a precipitate.

PAA208365

Distributed by Hospira, Inc.
Lake Forest, IL 60045 USA

Hospira